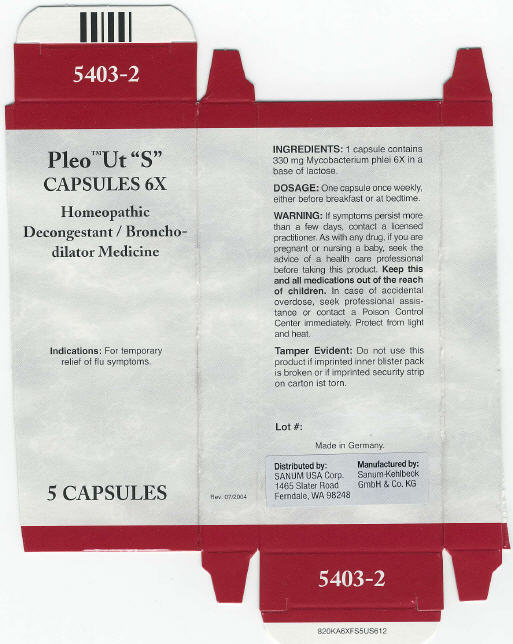 DRUG LABEL: Pleo Ut S
NDC: 60681-5403 | Form: CAPSULE
Manufacturer: Sanum Kehlbeck GmbH & Co. KG
Category: homeopathic | Type: HUMAN OTC DRUG LABEL
Date: 20091008

ACTIVE INGREDIENTS: mycobacterium phlei 6 [hp_X]/1 1
INACTIVE INGREDIENTS: lactose

Pleo™ Ut "S"
CAPSULES 6X

Homeopathic Decongestant / Bronchodilator Medicine

5 CAPSULES

Indications

For temporary relief of flu symptoms.

INGREDIENTS

1 capsule contains 330 mg Mycobacterium phlei 6X in a base of lactose.

DOSAGE

One capsule once weeky, either before breakfast or at bedtime.

WARNING

If symptoms persist more than a few days, contact a licensed practitioner. As with any drug, if you are pregnant or nursing a baby, seek the advice of a health care professional before taking this product.

KEEP OUT OF REACH OF CHILDREN

Keep this and all medications out of the reach of children. In case of accidental overdose, seek professional assistance or contact a Poison Control Center immediately.

STORAGE AND HANDLING

Protect from light and heat.

Tamper Evident

Do not use this product if imprinted inner blister pack is broken or if imprinted security strip on carton ist torn.

Made in Germany.

Distributed by:
SANUM USA Corp.
1465 Slater Road
Ferndale, WA 98248

Manufactured by:
Sanum-Kehlbeck
GmbH & Co. KG

Rev. 07/2004

PRINCIPAL DISPLAY PANEL - 5 Capsules Carton

Pleo™ Ut "S"
CAPSULES 6X

Homeopathic
Decongestant / Broncho-
dilator Medicine

Indications: For temporary
relief of flu symptoms.

5 CAPSULES